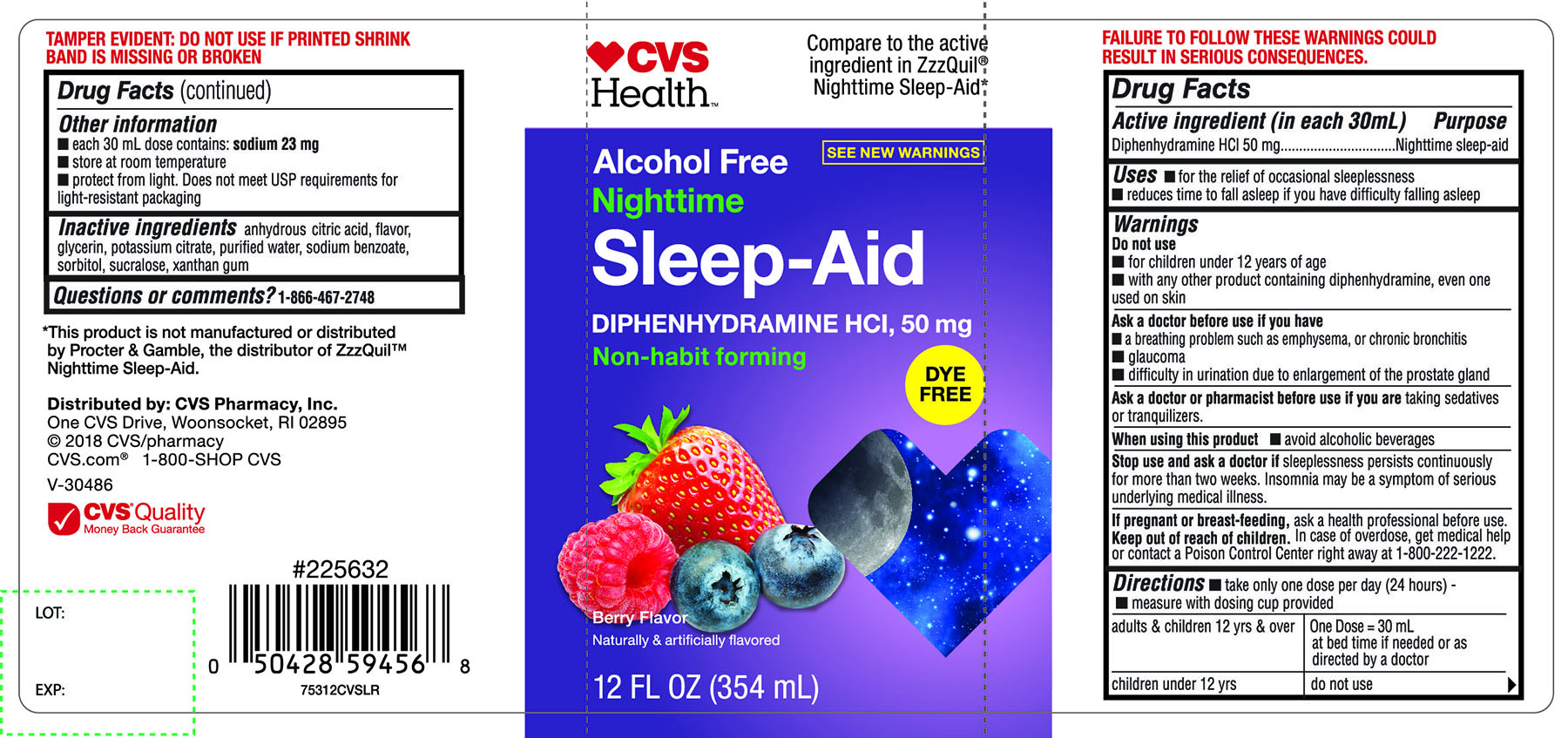 DRUG LABEL: CVS Health Nighttime Sleep Aid
NDC: 69842-753 | Form: LIQUID
Manufacturer: CVS Pharmacy,Inc.
Category: otc | Type: HUMAN OTC DRUG LABEL
Date: 20171018

ACTIVE INGREDIENTS: DIPHENHYDRAMINE HYDROCHLORIDE 50 mg/30 mL
INACTIVE INGREDIENTS: ANHYDROUS CITRIC ACID; GLYCERIN; POTASSIUM CITRATE; WATER; SODIUM BENZOATE; SORBITOL; SUCRALOSE; XANTHAN GUM

CVS Health™ Nighttime Sleep-Aid Diphenhydramine HCl Alcohol Free Dye-Free Berry Flavor 12 FL OZ (354 mL)

Drug Facts

Active ingredient (in each 30 mL)

Diphenhydramine HCl 50 mg

Purpose

Nighttime sleep-aid

Uses

- for the relief of occasional sleeplessness
- reduces time to fall asleep if you have difficulty falling asleep

Warnings

Do not use

- for children under 12 years of age
- with any other product containing diphenhydramine, even one used on skin

Ask a doctor before use if you have

- a breathing problem such as emphysema, or chronic bronchitis
- glaucoma
- difficulty in urination due to enlargement of the prostate gland

Ask a doctor or pharmacist before use if you are taking sedatives or tranquilizers

When using this product

- avoid alcoholic beverages

Stop use and ask a doctor if sleeplessness persists continuously for more than two weeks. Insomnia may be a symptom of serious underlying medical illness.

PREGNANCY OR BREAST FEEDING

If pregnant or breast-feeding, ask a health professional before use.

Keep out of reach of children.

In case of overdose, get medical help or contact a Poison Control Center right away at 1-800-222-1222.

Directions

- take only one dose per day (24 hours)
- Measure with dosing cup provided

adults & children 12 yrs & over | One Dose = 30 mL at bed time if needed or as directed by a doctor
Children under 12 yrs | do not use

Other information

- each 30 mL dose contains: sodium 23 mg
- store at room temperature
- protect from light. Does not meet USP requirements for light-resistant packaging

Inactive ingredients

anhydrous citric acid, flavor, glycerin, potassium citrate, purified water, sodium benzoate, sorbitol, sucralose, xanthan gum.

Questions or comments?

1-866-467-2748

PRINCIPAL DISPLAY PANEL

CVS Health™

Compare to the active ingredient in ZzzQuil® Nighttime Sleep-Aid

NDC 69842-753-12

Alcohol Free

Nighttime

Sleep-Aid

Diphenhydramine HCl, 50 mg

Non – habit forming

DYE FREE

BERRY FLAVOR

12 FL OZ (354 mL)

SEE NEW WARNINGS.

FAILURE TO FOLLOW THESE WARNINGS COULD RESULT IN SERIOUS CONSEQUENCES.

TAMPER EVIDENT: DO NOT USE IF PRINTED SHRINK BAND IS MISSING OR BROKEN

*This product is not manufactured or distributed by Procter & Gamble, the distributor of ZzzQuil™ Nighttime Sleep-Aid.

DISTRIBUTED BY: CVS Pharmacy, Inc.

One CVS Drive, Woonsocket, RI 02895

2018 CVS/ Pharmacy

CVS .com® 1-800-SHOP CVS

CVS Quality Money Back Guarantee